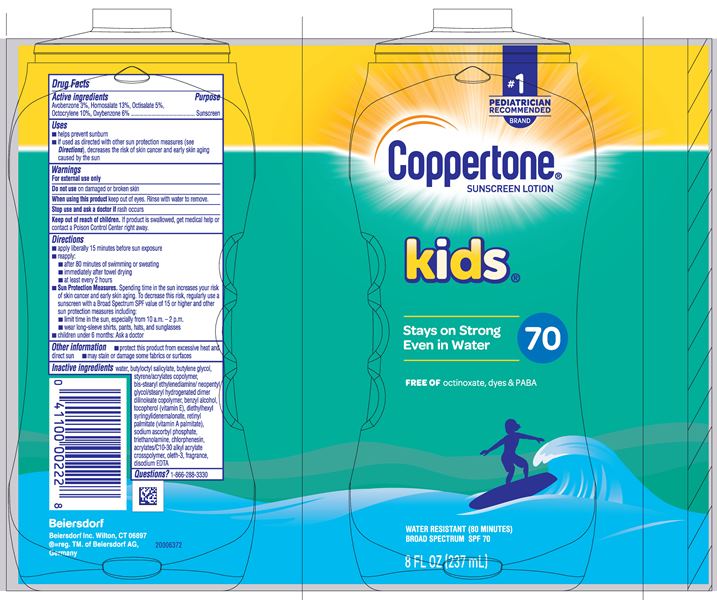 DRUG LABEL: Coppertone Kids Sunscreen SPF 70
NDC: 66800-2462 | Form: LOTION
Manufacturer: Beiersdorf Inc
Category: otc | Type: HUMAN OTC DRUG LABEL
Date: 20251231

ACTIVE INGREDIENTS: OXYBENZONE 6 g/100 g; AVOBENZONE 3 g/100 g; HOMOSALATE 13 g/100 g; OCTISALATE 5 g/100 g; OCTOCRYLENE 10 g/100 g
INACTIVE INGREDIENTS: BUTYLENE GLYCOL; WATER; TOCOPHEROL; SODIUM ASCORBYL PHOSPHATE; CHLORPHENESIN; TROLAMINE; VITAMIN A PALMITATE; FRAGRANCE FLORAL ORC0902236; EDETATE DISODIUM ANHYDROUS; ACRYLATES CROSSPOLYMER-6; OLETH-3; DIETHYLHEXYL SYRINGYLIDENEMALONATE; BUTYLOCTYL SALICYLATE; BENZYL ALCOHOL; ETHYLENE DISTEARAMIDE

Kids Lotion SPF 70

Active ingredients

Avobenzone 3%, Homosalate 13%, Octisalate 5%, Octocrylene 10%, Oxybenzone 6%

Purpose

Sunscreen

Uses

■ helps prevent sunburn

■ if used as directed with other sun protection measures (see Directions), decreases the risk of skin cancer and early skin aging caused by the sun

Warnings

For external use only

Do not useon damaged or broken skin

WHEN USING

When using this productkeep out of eyes. Rinse with water to remove.

Stop use and ask a doctor ifrash occurs

Keep out of reach of children.If product is swallowed, get medical help or contact a Poison Control Center right away.

Directions

■ apply liberally 15 minutes before sun exposure

■ reapply:

■ after 80 minutes of swimming or sweating

■ immediately after towel drying

■ at least every 2 hours

■ Sun Protection Measures.Spending time in the sun increases your risk of skin cancer and early skin aging. To decrease this risk, regularly use a sunscreen with a Broad Spectrum SPF value of 15 or higher and other sun protection measures including:

■ limit time in the sun, especially from 10 a.m. – 2 p.m.

■ wear long-sleeve shirts, pants, hats, and sunglasses

■ children under 6 months: Ask a doctor

Other information

■ protect this product from excessive heat and direct sun

■ may stain or damage some fabrics or surfaces

Inactive ingredients

water, butyloctyl salicylate, butylene glycol, styrene/acrylates copolymer, bis-stearyl ethylenediamine/neopentyl glycol/stearyl hydrogenated dimer dilinoleate copolymer, benzyl alcohol, tocopherol (vitamin E), diethylhexyl syringylidenemalonate, retinyl palmitate (vitamin A palmitate), sodium ascorbyl phosphate, triethanolamine, chlorphenesin, acrylates/C10-30 alkyl acrylate crosspolymer, oleth-3, fragrance, disodium EDTA

Questions

1-866-288-3330

PACKAGE LABEL

Coppertone Sunscreen Lotion

kids

Stays on Strong Even in Water

70

Free of Octinoxate, Dyes, PABA

Water Resistant (80 Minutes)

Broad Spectrum SPF 70